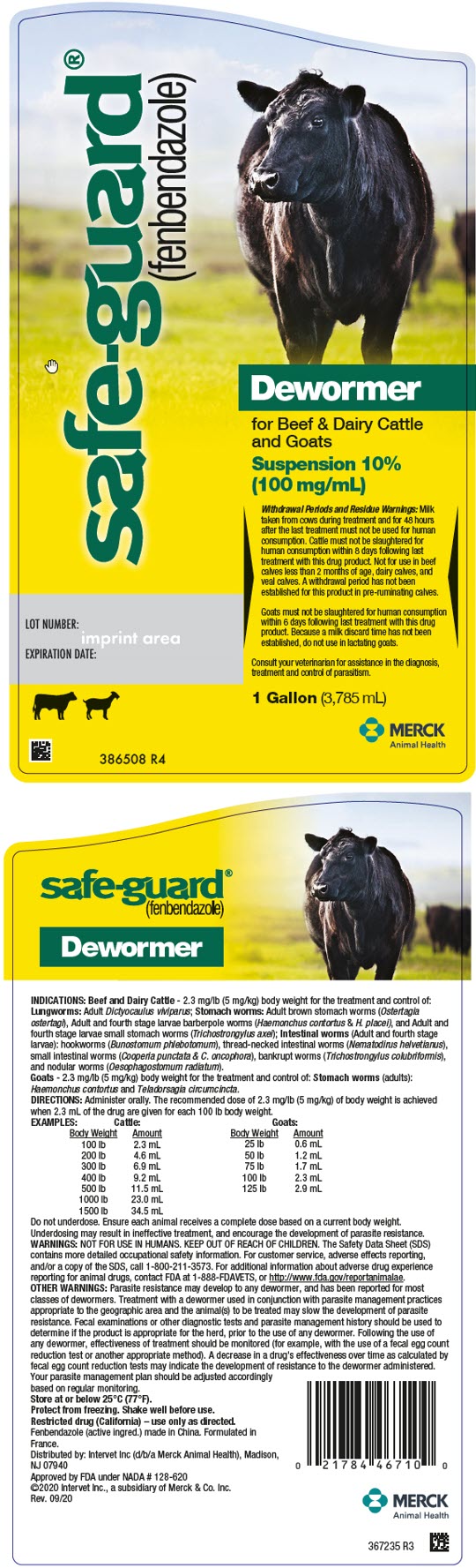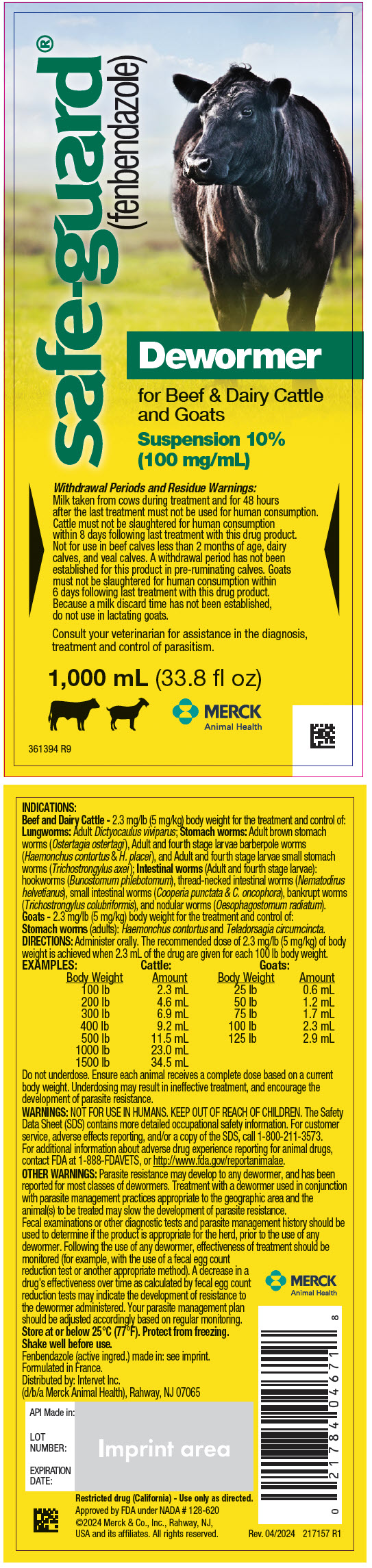 DRUG LABEL: Safe-Guard
NDC: 57926-088 | Form: SUSPENSION
Manufacturer: Merck Sharp & Dohme Corp.
Category: animal | Type: OTC ANIMAL DRUG LABEL
Date: 20241120

ACTIVE INGREDIENTS: FENBENDAZOLE 100 mg/1 mL

safe-guard®
(fenbendazole)
Dewormer

INDICATIONS:

Beef and Dairy Cattle - 2.3 mg/lb (5 mg/kg) body weight for the treatment and control of: Lungworms: Adult Dictyocaulus viviparus; Stomach worms: Adult brown stomach worms (Ostertagia ostertagi), Adult and fourth stage larvae barberpole worms (Haemonchus contortus & H. placei), and Adult and fourth stage larvae small stomach worms (Trichostrongylus axei); Intestinal worms (Adult and fourth stage larvae): hookworms (Bunostomum phlebotomum), thread-necked intestinal worms (Nematodirus helvetianus), small intestinal worms (Cooperia punctata & C. oncophora), bankrupt worms (Trichostrongylus colubriformis), and nodular worms (Oesophagostomum radiatum).

Goats - 2.3 mg/lb (5 mg/kg) body weight for the treatment and control of: Stomach worms (adults): Haemonchus contortus and Teladorsagia circumcincta.

DOSAGE AND ADMINISTRATION

DIRECTIONS: Administer orally. The recommended dose of 2.3 mg/lb (5 mg/kg) of body weight is achieved when 2.3 mL of the drug are given for each 100 lb body weight.

EXAMPLES:

Cattle: |  |  | Goats:
Body Weight | Amount |  | Body Weight | Amount
100 lb | 2.3 mL |  | 25 lb | 0.6 mL
200 lb | 4.6 mL |  | 50 lb | 1.2 mL
300 lb | 6.9 mL |  | 75 lb | 1.7 mL
400 lb | 9.2 mL |  | 100 lb | 2.3 mL
500 lb | 11.5 mL |  | 125 lb | 2.9 mL
1000 lb | 23.0 mL
1500 lb | 34.5 mL

Do not underdose. Ensure each animal receives a complete dose based on a current body weight. Underdosing may result in ineffective treatment, and encourage the development of parasite resistance.

WARNINGS

WARNINGS: NOT FOR USE IN HUMANS. KEEP OUT OF REACH OF CHILDREN. The Safety Data Sheet (SDS) contains more detailed occupational safety information. For customer service, adverse effects reporting, and/or a copy of the SDS, call 1-800-211-3573. For additional information about adverse drug experience reporting for animal drugs, contact FDA at 1-888-FDAVETS, or http://www.fda.gov/reportanimalae.

WARNINGS

OTHER WARNINGS: Parasite resistance may develop to any dewormer, and has been reported for most classes of dewormers. Treatment with a dewormer used in conjunction with parasite management practices appropriate to the geographic area and the animal(s) to be treated may slow the development of parasite resistance.

Fecal examinations or other diagnostic tests and parasite management history should be used to determine if the product is appropriate for the herd, prior to the use of any dewormer. Following the use of any dewormer, effectiveness of treatment should be monitored (for example, with the use of a fecal egg count reduction test or another appropriate method). A decrease in a drug's effectiveness over time as calculated by fecal egg count reduction tests may indicate the development of resistance to the dewormer administered. Your parasite management plan should be adjusted accordingly based on regular monitoring.

STORAGE AND HANDLING

Store at or below 25°C (77°F). Protect from freezing.

Shake well before use.

Fenbendazole (active ingred.) made in: see imprint.
Formulated in France.
Distributed by: Intervet Inc.
(d/b/a Merck Animal Health), Rahway, NJ 07065

Restricted drug (California) - Use only as directed.

Approved by FDA under NADA # 128-620

©2024 Merck & Co., Inc., Rahway, NJ,
USA and its affiliates. All rights reserved.

Rev. 04/2024
217157 R1

PRINCIPAL DISPLAY PANEL - 3,785 mL Bottle Label

safe-guard®
(fenbendazole)

Dewormer

for Beef & Dairy Cattle
and Goats

Suspension 10%
(100 mg/mL)

Withdrawal Periods and Residue Warnings: Milk
taken from cows during treatment and for 48 hours
after the last treatment must not be used for human
consumption. Cattle must not be slaughtered for
human consumption within 8 days following last
treatment with this drug product. Not for use in beef
calves less than 2 months of age, dairy calves, and
veal calves. A withdrawal period has not been
established for this product in pre-ruminating calves.
Goats must not be slaughtered for human consumption
within 6 days following last treatment with this drug
product. Because a milk discard time has not been
established, do not use in lactating goats.

Consult your veterinarian for assistance in the diagnosis,
treatment and control of parasitism.

1 Gallon (3,785 mL)

MERCK
Animal Health

LOT NUMBER:
EXPIRATION DATE:

386508 R4

PRINCIPAL DISPLAY PANEL - 1,000 mL Bottle Label

safe-guard®
(fenbendazole)

Dewormer

for Beef & Dairy Cattle
and Goats

Suspension 10%
(100 mg/mL)

Withdrawal Periods and Residue Warnings:
Milk taken from cows during treatment and for 48 hours
after the last treatment must not be used for human consumption.
Cattle must not be slaughtered for human consumption
within 8 days following last treatment with this drug product.
Not for use in beef calves less than 2 months of age, dairy
calves, and veal calves. A withdrawal period has not been
established for this product in pre-ruminating calves. Goats
must not be slaughtered for human consumption within
6 days following last treatment with this drug product.
Because a milk discard time has not been established,
do not use in lactating goats.

Consult your veterinarian for assistance in the diagnosis,
treatment and control of parasitism.

1,000 mL (33.8 fl oz)

MERCK
Animal Health

361394 R9